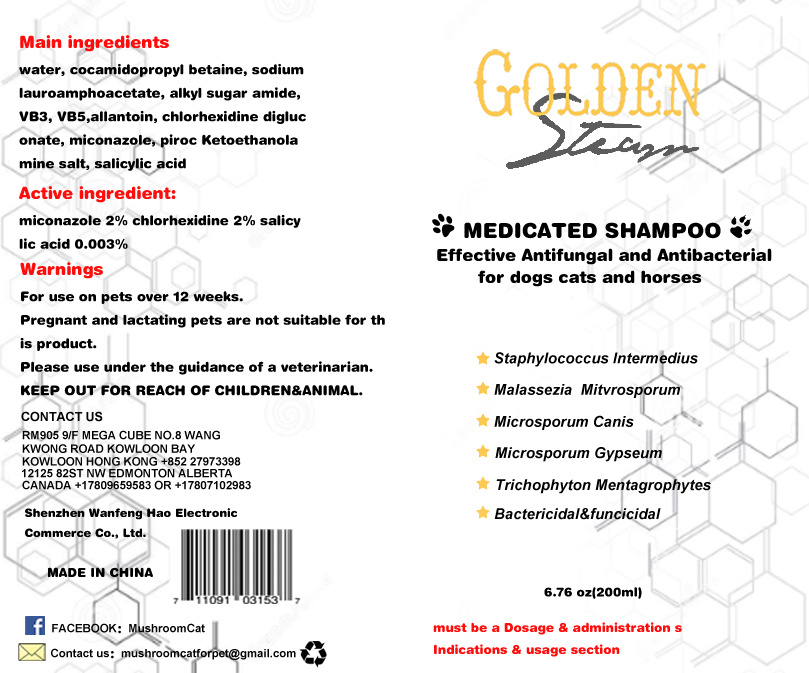 DRUG LABEL: MedicatedShampoo
NDC: 40738-001 | Form: LIQUID
Manufacturer: Shenzhen Wanfeng Hao Electronic Commerce Co., Ltd.
Category: animal | Type: OTC ANIMAL DRUG LABEL
Date: 20191120

ACTIVE INGREDIENTS: MICONAZOLE 0.02 1/1 1; SALICYLIC ACID 0.02 1/1 1; CHLORHEXIDINE GLUCONATE 0.00003 1/1 1
INACTIVE INGREDIENTS: SODIUM LAUROAMPHOACETATE; CALCIUM PANTOTHENATE; NIACIN; WATER; PIROCTONE OLAMINE; COCO/OLEAMIDOPROPYL BETAINE

WARNINGS AND PRECAUTIONS

For external use only. Flammable. Keep out the reach of children. If ingested call for medical help. Keep away from fire or flame.

VETERINARY USE ONLY